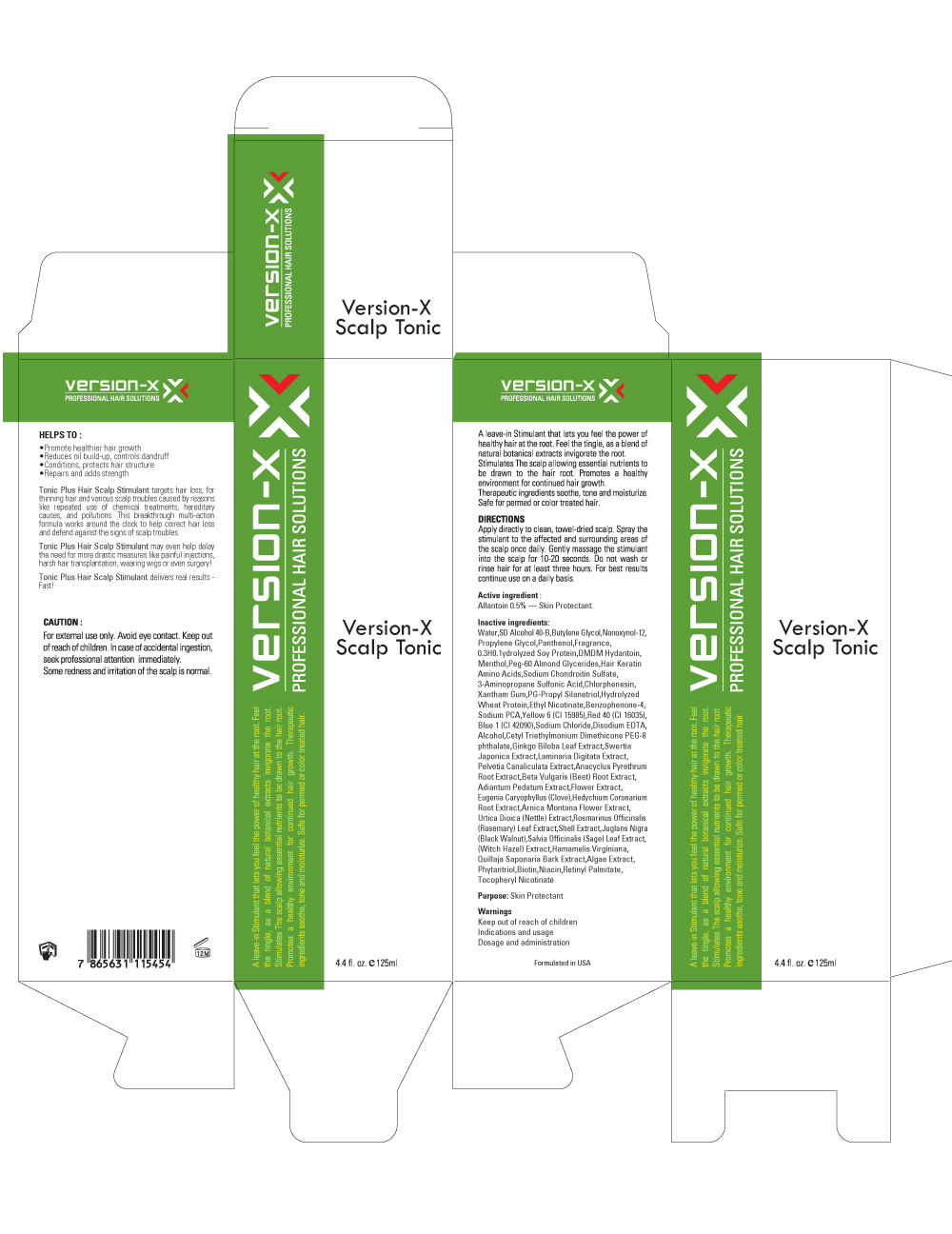 DRUG LABEL: Version X Scalp Tonic
NDC: 58069-010 | Form: LIQUID
Manufacturer: CHRISTLTD
Category: otc | Type: HUMAN OTC DRUG LABEL
Date: 20130521

ACTIVE INGREDIENTS: Allantoin 0.625 mg/125 mL
INACTIVE INGREDIENTS: Water; Butylene Glycol; Panthenol

ACTIVE INGREDIENT

Active ingredient: Allantoin 0.5%

INACTIVE INGREDIENT

Inactive ingredients:
Water,SD Alcohol 40-B,Butylene Glycol,Nonoxynol-12,Propylene Glycol,Panthenol,Fragrance,0.3H0.1ydrolyzed Soy Protein,DMDM Hydantoin,Menthol,Peg-60 Almond Glycerides,Hair Keratin, Amino Acids,Sodium Chondroitin Sulfate,3-Aminopropane Sulfonic Acid,Chlorphenesin, Xantham Gum,PG-Propyl Silanetriol,Hydrolyzed Wheat Protein,Ethyl Nicotinate,Benzophenone-4, Sodium PCA,Yellow 6 (CI 15985),Red 40 (CI 16035),Blue 1 (CI 42090),Sodium Chloride,Disodium EDTA,Alcohol,Cetyl Triethylmonium Dimethicone PEG-8phthalate,Ginkgo Biloba Leaf Extract,Swertia Japonica Extract,Laminaria Digitata Extract,Pelvetia Canaliculata Extract,Anacyclus Pyrethrum, Root Extract,Beta Vulgaris (Beet) Root Extract,Adiantum Pedatum Extract,Flower Extract, Eugenia Caryophyllus (Clove),Hedychium CoronariumRoot Extract,Arnica Montana Flower Extract, Urtica Dioica (Nettle) Extract,Rosmarinus Officinalis(Rosemary) Leaf Extract,Shell Extract,Juglans Nigra(Black Walnut),Salvia Officinalis (Sage) Leaf Extract, Hamamelis Virginiana,Quillaja Saponaria Bark Extract,Algae Extract,Phytantriol,Biotin,Niacin,Retinyl Palmitate, Tocopheryl Nicotinate

PURPOSE

Purpose: Skin Protectant

WARNINGS

CAUTION:
For external use only.
Avoid eye contact.
Keep out of reach children.
In case of accidental ingestion, seek professional attention immediately.
Some redness and iffitation of the scalp is nomal

KEEP OUT OF REACH OF CHILDREN

INDICATIONS AND USAGE

DIRECTIONS
Apply directly to clean, towel-dried scalp.
Spray the stimulant to the affected and surrounding areas of the scalp once daily.
Gently massage the stimulant into the scalp for 10-20 seconds.
Do not wash or rinse hair for at least three hours. For best results continue use on a daily basis.

DOSAGE AND ADMINISTRATION

DIRECTIONS
Apply directly to clean, towel-dried scalp.
Spray the stimulant to the affected and surrounding areas of the scalp once daily.
Gently massage the stimulant into the scalp for 10-20 seconds.
Do not wash or rinse hair for at least three hours. For best results continue use on a daily basis.